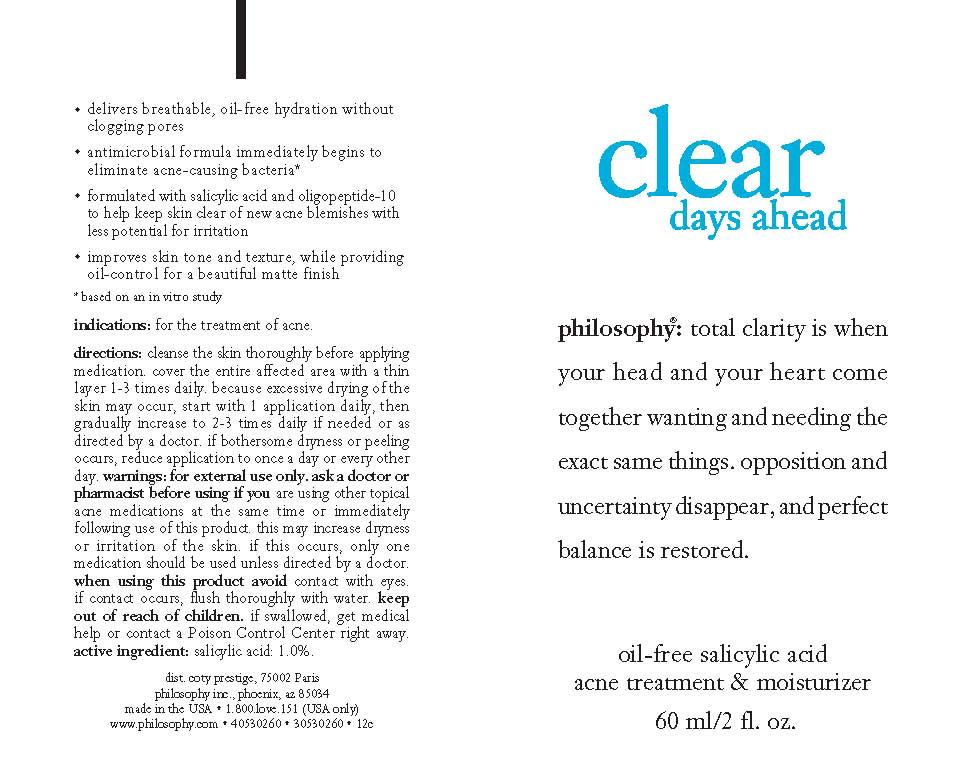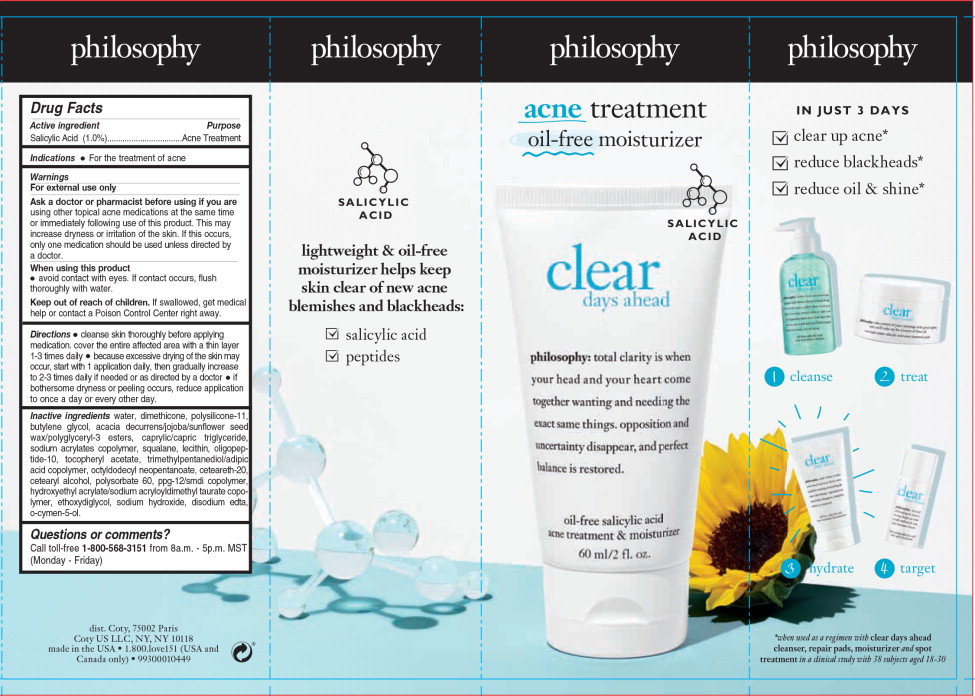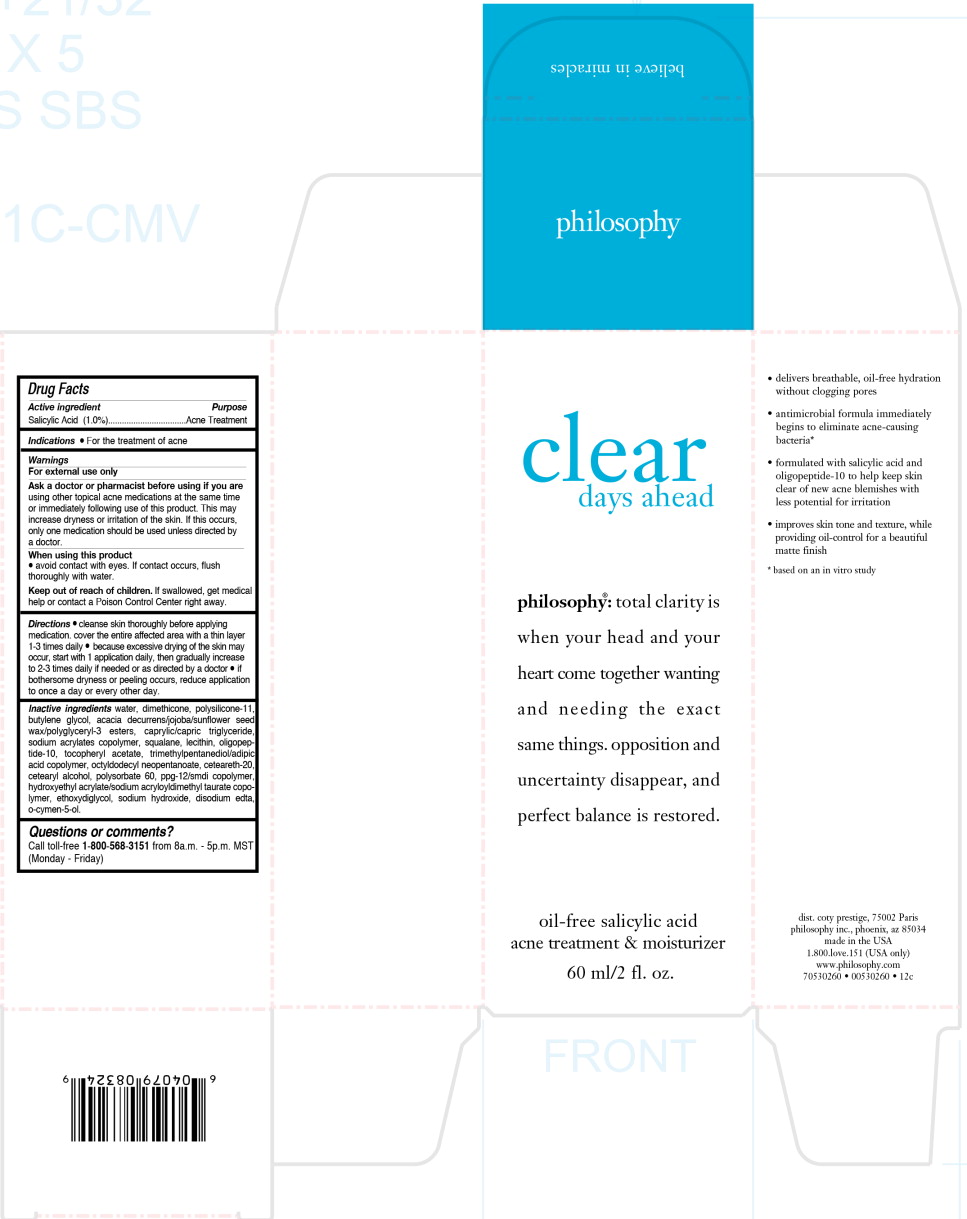 DRUG LABEL: clear days ahead
NDC: 50184-1010 | Form: CREAM
Manufacturer: Philosophy Inc.
Category: otc | Type: HUMAN OTC DRUG LABEL
Date: 20251217

ACTIVE INGREDIENTS: SALICYLIC ACID 0.6 g/60 mL
INACTIVE INGREDIENTS: WATER; DIMETHICONE; MEDIUM-CHAIN TRIGLYCERIDES; SQUALANE; .ALPHA.-TOCOPHEROL ACETATE; OCTYLDODECYL NEOPENTANOATE; POLYOXYL 20 CETOSTEARYL ETHER; CETOSTEARYL ALCOHOL; POLYSORBATE 60; DIETHYLENE GLYCOL MONOETHYL ETHER; SODIUM HYDROXIDE; EDETATE DISODIUM; O-CYMEN-5-OL

Drug Facts

Active ingredient

Salicylic Acid (1.0%)

Purpose

Acne Treatment

Indications

- For the treatment of acne

Warnings

For external use only

Ask a doctor or pharmacist before using if you are using other topical acne medications at the same time or immediately following use of this product. This may increase dryness or irritation of the skin. If this occurs, only one medication should be used unless directed by a doctor.

When using this product

- avoid contact with eyes. If contact occurs, flush thoroughly with water.

Keep out of reach of children.

If swallowed, get medical help or contact a Poison Control Center right away.

Directions

- cleanse skin thoroughly before applying medication. cover the entire affected area with a thin layer 1-3 times daily
- because excessive drying of the skin may occur, start with 1 application daily, then gradually increase to 2-3 times daily if needed or as directed by a doctor
- if bothersome dryness or peeling occurs, reduce application to once a day or every other day.

Inactive ingredients

water, dimethicone, polysilicone-11, butylene glycol, acacia decurrens/jojoba/sunflower seed wax/polyglyceryl-3 esters, caprylic/capric triglyceride, sodium acrylates copolymer, squalane, lecithin, oligopeptide- 10, tocopheryl acetate, trimethylpentanediol/adipic acid copolymer, octyldodecyl neopentanoate, ceteareth-20, cetearyl alcohol, polysorbate 60, ppg-12/smdi copolymer, hydroxyethyl acrylate/sodium acryloyldimethyl taurate copolymer, ethoxydiglycol, sodium hydroxide, disodium edta, o-cymen-5-ol.

Questions or comments?

Call toll-free 1-800-568-3151 from 8a.m. - 5p.m. MST (Monday - Friday)

Principal Display Panel - 60 ml Sleeve Label

philosophy

acne treatment

oil-free moisturizer

salicylic acid

Principal Display Panel - 60 ml Box Label

clear

days ahead

philosophy®: total clarity is
when your head and your
heart come together wanting
and needing the exact
same things. opposition and
uncertainty disappear, and
perfect balance is restored.

oil-free salicylic acid

acne treatment & moisturizer

60 ml/2 fl. oz.

Principal Display Panel - 60 ml Bottle Label

clear

days ahead

philosophy®: total clarity is when
your head and your heart come
together wanting and needing the
exact same things. opposition and
uncertainty disappear, and perfect
balance is restored.

oil-free salicylic acid

acne treatment & moisturizer

60 ml/2 fl. oz.